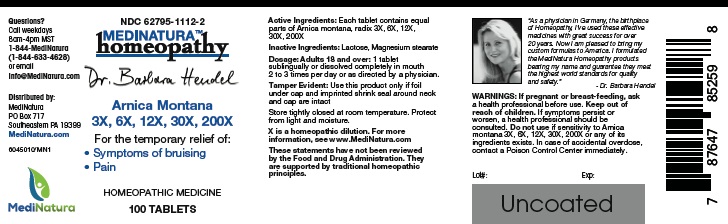 DRUG LABEL: Arnica Montana 3X, 6X, 12X, 30X, 200X
NDC: 62795-1112 | Form: TABLET
Manufacturer: MediNatura Inc
Category: homeopathic | Type: HUMAN OTC DRUG LABEL
Date: 20220818

ACTIVE INGREDIENTS: ARNICA MONTANA ROOT 3 [hp_X]/1 1
INACTIVE INGREDIENTS: LACTOSE MONOHYDRATE; MAGNESIUM STEARATE

Dr. Hendel Arnica Montana 3X, 6X, 12X, 30X, 200X Tablet

WARNINGS

If pregnant or breast-feeding, ask a health professional before use. Keep out of reach of children. If symptoms persist or

worsen, a health professional should be consulted. Do not use if sensitivity to Hendel Arnica montana 3X, 6X, 12X, 30X, 200X or any of its ingredients exists. In case of accidental overdose, contact a Poison Control Center immediately

KEEP OUT OF REACH OF CHILDREN

INDICATIONS

• Symptoms of bruising

• Pain

ACTIVE INGREDIENT

Arnica Montana 3X, 6X, 12X, 30X, 200X

INACTIVE INGREDIENT

Lactose, Magnesium stearate

DIRECTIONS

Dosage: Adults 18 and over: 1 tablet sublingually or dissolved completely in mouth 2 to 3 times per day or as directed by a physician.

USES

For the temporary relief of:

• Symptoms of bruising

• Pain

PACKAGE LABEL

Add image transcription here...